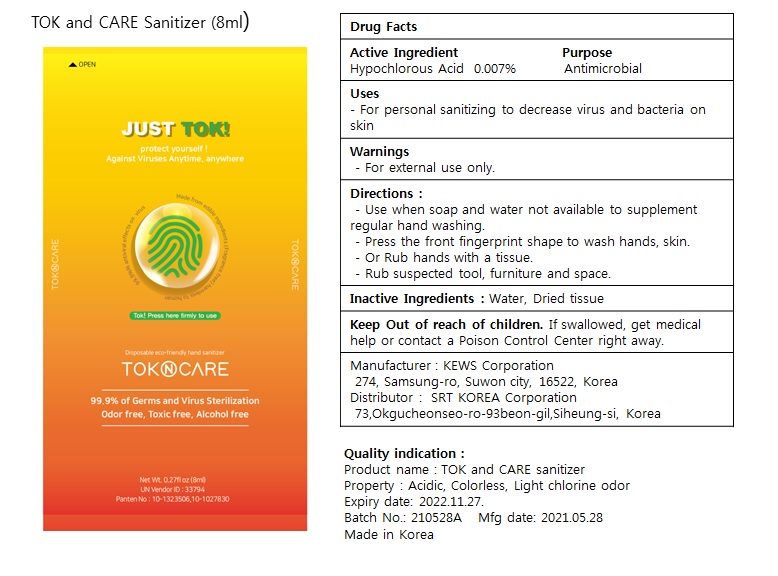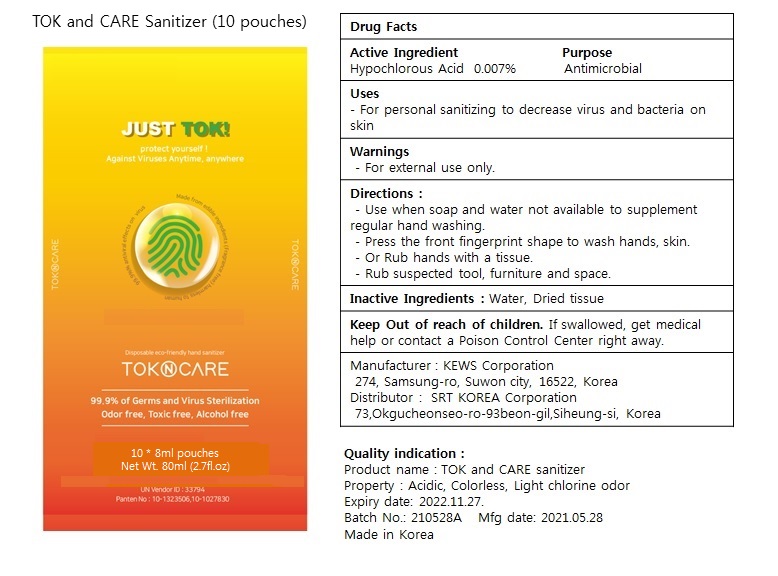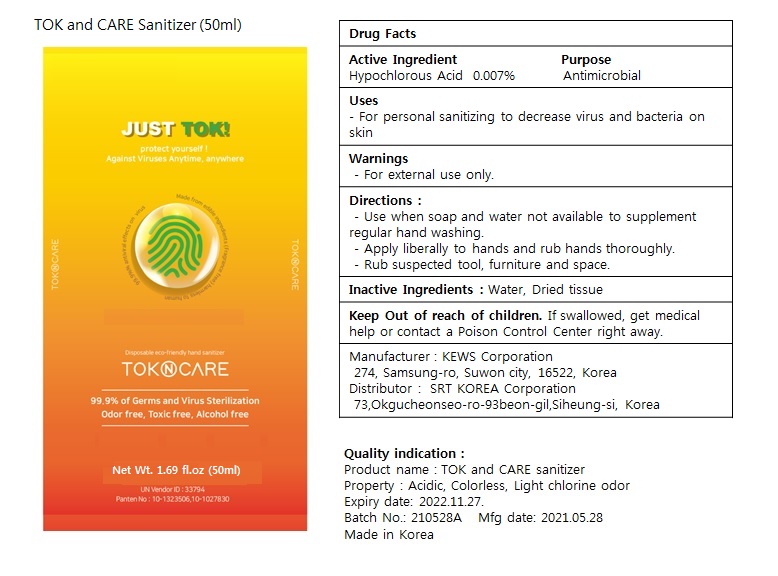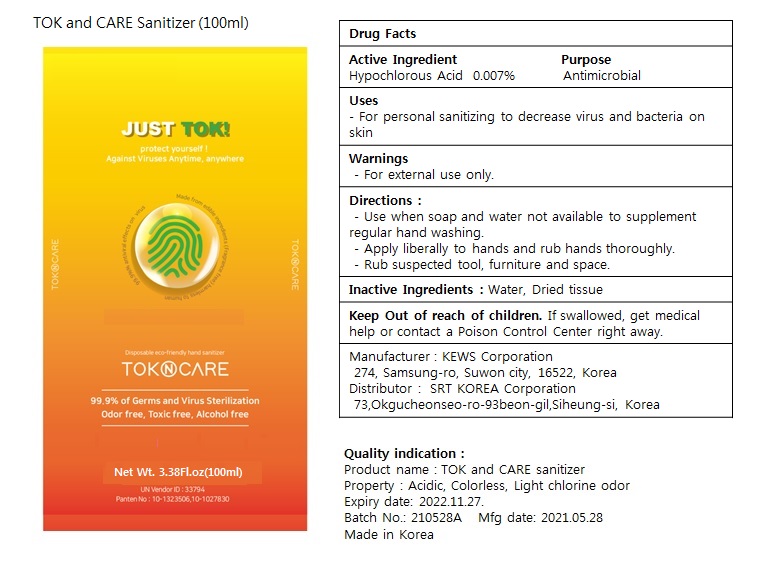 DRUG LABEL: TOK AND CARE SANITIZER
NDC: 75644-004 | Form: LIQUID
Manufacturer: KEWS CORPORATION
Category: otc | Type: HUMAN OTC DRUG LABEL
Date: 20210615

ACTIVE INGREDIENTS: HYPOCHLOROUS ACID 0.007 mg/1 mL
INACTIVE INGREDIENTS: WATER

TOK AND CARE SANITIZER

Active Ingredient

Hypochlorous Acid ------ 0.0.007%

Purpose

Antimicrobial

Directions:

Use when soap and water not available to supplement regular hand washing.

Press the front fingerprint shape to wash hands, skin.

Or rub hands with a tissue

Rub suspected tool, furniture, and space.

Inactive Ingredient(s)

Water

Intended Use

For Personal sanitizing to decrease virus and baceteria on skin

Warnings:

For external use only

Purpose:

For personal sanitizing to decrease virus and bacteria on skin

Keep out of reach of children.

If swallowed, get medical help or contact a Poison Control Center right away.

0.27 fl oz (8 mL) PDP

0.27 fl oz (8mL) NDC 75644-004-01

0.27fl oz (8ml ea) X 10 Pouches PDP

0.27 fl oz (8ml) X 10 Pouches NDC 75644-004-02

1.69 fl oz (50ml) PDP 75644-004-03

3.38 Fl oz (100ml) PDP, NDC: 75644-004-04